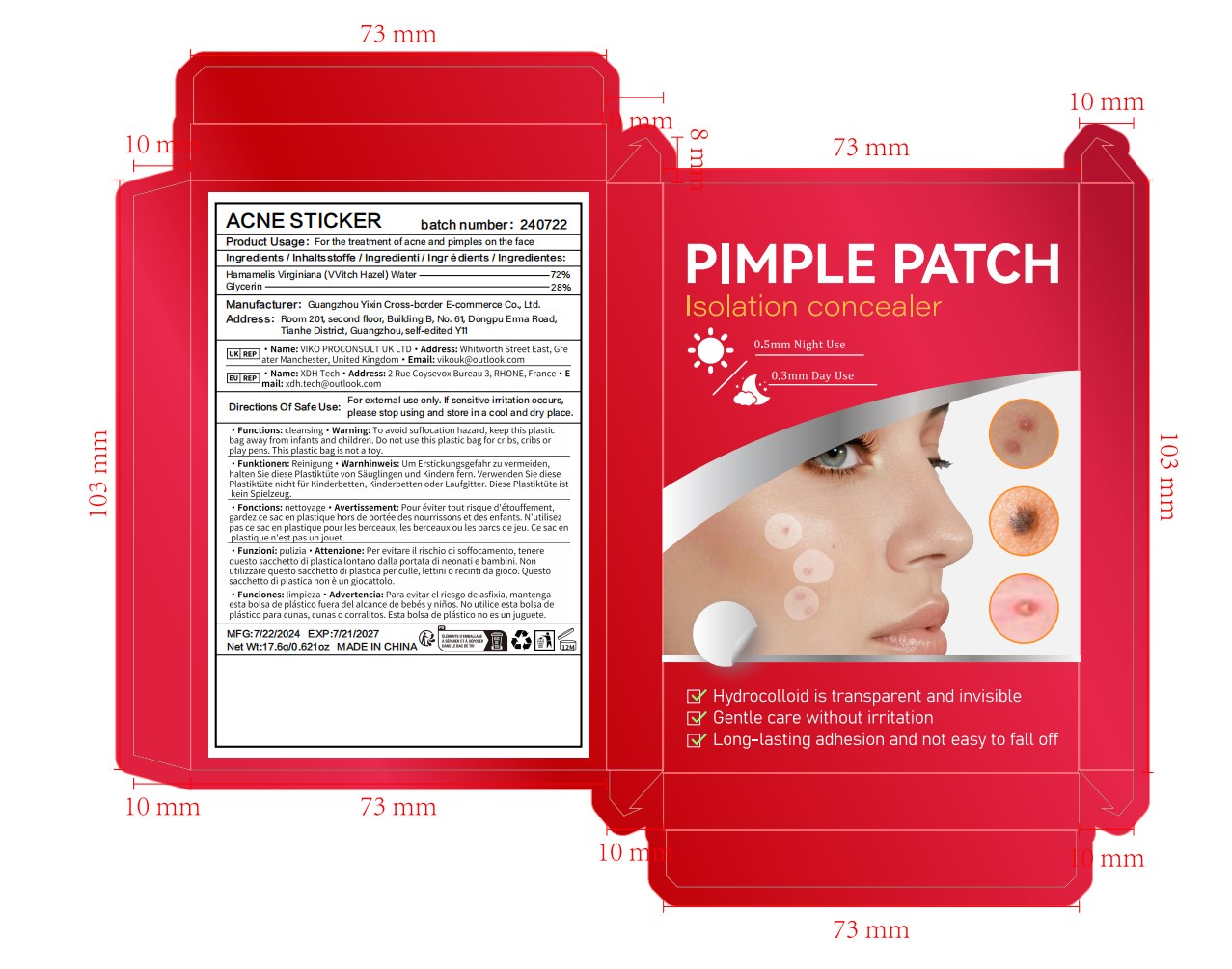 DRUG LABEL: Acne patch
NDC: 84778-004 | Form: PATCH
Manufacturer: Guangzhou Yixin Cross-border E-commerce Co., Ltd.
Category: otc | Type: HUMAN OTC DRUG LABEL
Date: 20241004

ACTIVE INGREDIENTS: HAMAMELIS VIRGINIANA TOP WATER 7.2 g/100 g
INACTIVE INGREDIENTS: GLYCERIN

COMPONENTS

Hamamelis Virginiana (VVitch Hazel) Water 7.2%

PURPOSE

For the treatment of acne and pimples on the face

INDICATIONS AND USAGE

Clean your skin first, choose a suitable size and stick it on the acne, wait for a few hours, and then wash it with warm water

WARNINGS

For external use only.

If sensitive irritation occurs, please stop using and store in a cool and dry place.

DOSAGE AND ADMINISTRATION

For external use only.

DO NOT USE

Please make sure your skin is clean before use. Avoid using on open wounds or skin with allergic reactions.

WHEN USING

Clean the skin with warm water to ensure that the skin surface is clean. Choose the appropriate size of acne patch that can completely cover the acne. Let the acne patch stay on the skin for a sufficient time. After the use time is over, you can clean the skin with warm water.

Do not use on open wounds or allergic skin.

KEEP OUT OF REACH OF CHILDREN

If sxralowed, get medical help or contact a Poison Conirol Cenler ngiht away.

INACTIVE INGREDIENT

Glycerin